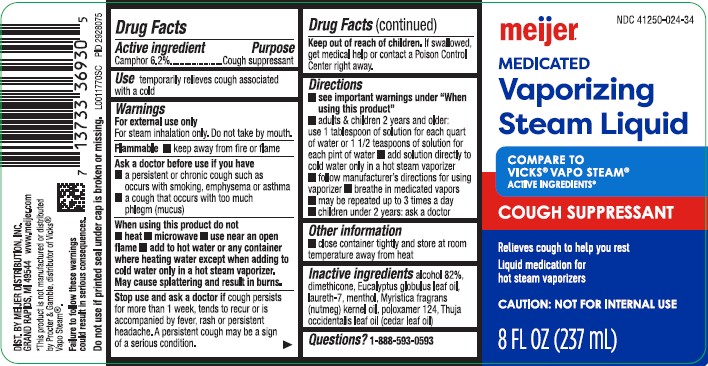 DRUG LABEL: Vaporizing
NDC: 41250-024 | Form: LIQUID
Manufacturer: Meijer, Inc.
Category: otc | Type: HUMAN OTC DRUG LABEL
Date: 20260219

ACTIVE INGREDIENTS: CAMPHOR (NATURAL) 62 mg/1 mL
INACTIVE INGREDIENTS: ALCOHOL; DIMETHICONE; EUCALYPTUS OIL; LAURETH-7; MENTHOL; NUTMEG OIL; POLOXAMER 124; CEDAR LEAF OIL

Meijer397.002/397AB
Medicated Vaporizing Steam Liquid

Active ingredient

Camphor 6.2%

Purpose

Cough suppressant

Use

temporarily relieves cough associated with a cold

Warnings

For External use only

For steam inhalation only. Do not take by mouth.

Flammable

- keep away from fire or flame

Ask a doctor

- a persistent or chronic cough such as occurs with smoking, emphysema or asthma
- a cough that occurs with too much phlegm (mucus)

When using this product do not

- heat
- microwave
- use near open flame
- add to hot water or any container where heating water except when adding to cold water only in a hot steam vaporizer.

May cause splattering and result in burns.

Stop use and ask a doctor if

cough persists for more than 1 week, tends to recur or is accompanied by fever, rash or persistant headache. A persistant cough may be a sign of a serious condition.

Keep out of reach of children.

If swallowed, get medical help or contact a Poison Control Center right away.

Directions

- see important warnings under "When using this product"
- adults and children 2 years and older: use 1 tablespoon of solution for each quart of water or 1 1/2 teaspoons of solution for each pint of water
- add solution directly to cold water only in a hot steam vaporizer
- follow manufacturer's directions for using vaporizer
- breathe in medicated vapors
- may be repeated up to 3 times a day
- children uner 2 years: ask a doctor

Other information

- close container tightly and store at room temperature away from heat

Inactive ingredients

alcohol 82%, dimethicone, Eucalyptus globulus leaf oil, laureth-7, menthol, Myristica fragrans (nutmeg) kernel oil,
poloxamer 124, Thuja occidentalis leaf oil (cedar leaf oil)

Questions?

1-888-593-0593

Adverse Reactoions

DIST. BY MEIJER DISTRIBUTION, INC.

GRAND RAPIDS, MI 49544

www.meijer.com

Disclaimer

*This product is not manufactured or distributed by Procter & Gamble, distributor of Vicks®Vapo Steam.

Warnings

Failure to follow these warnings could result in serious consequences.

Do not use if printed seal under cap is broken or missing.

Principal display panel

NDC 41250-024-34

meijer®

MEDICATED

Vaporizing

Steam Liquid

COMPARE TO VICKS®VAPO STEAM®ACTIVE INGREDIENTS*

COUGH SUPPRESSANT

Relieves cough to help you rest

Liquid medication for hot steam vaporizers

CAUTION: NOT FOR INTERNAL USE

8 FL OZ (237 mL)